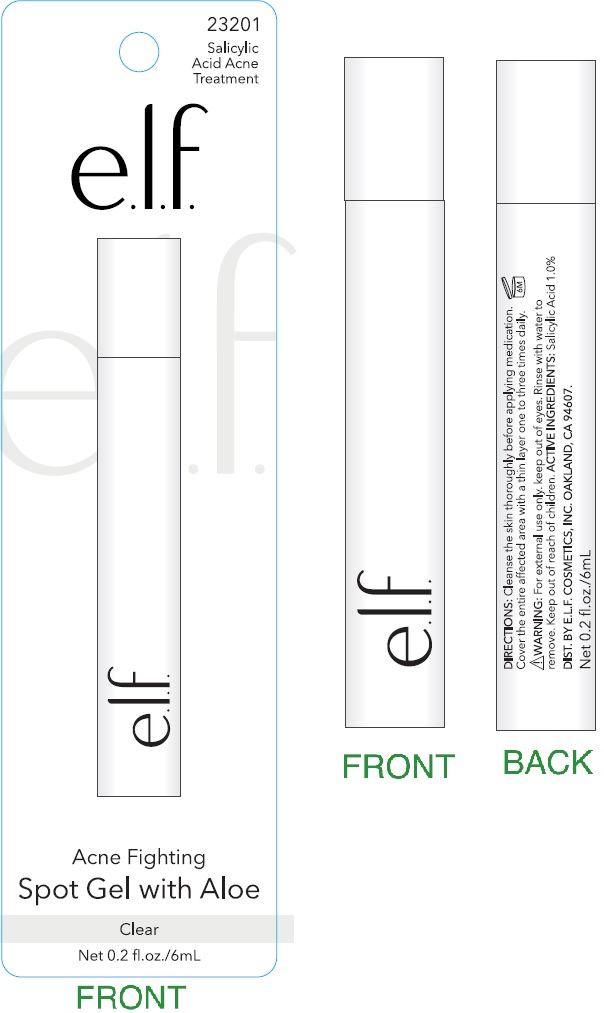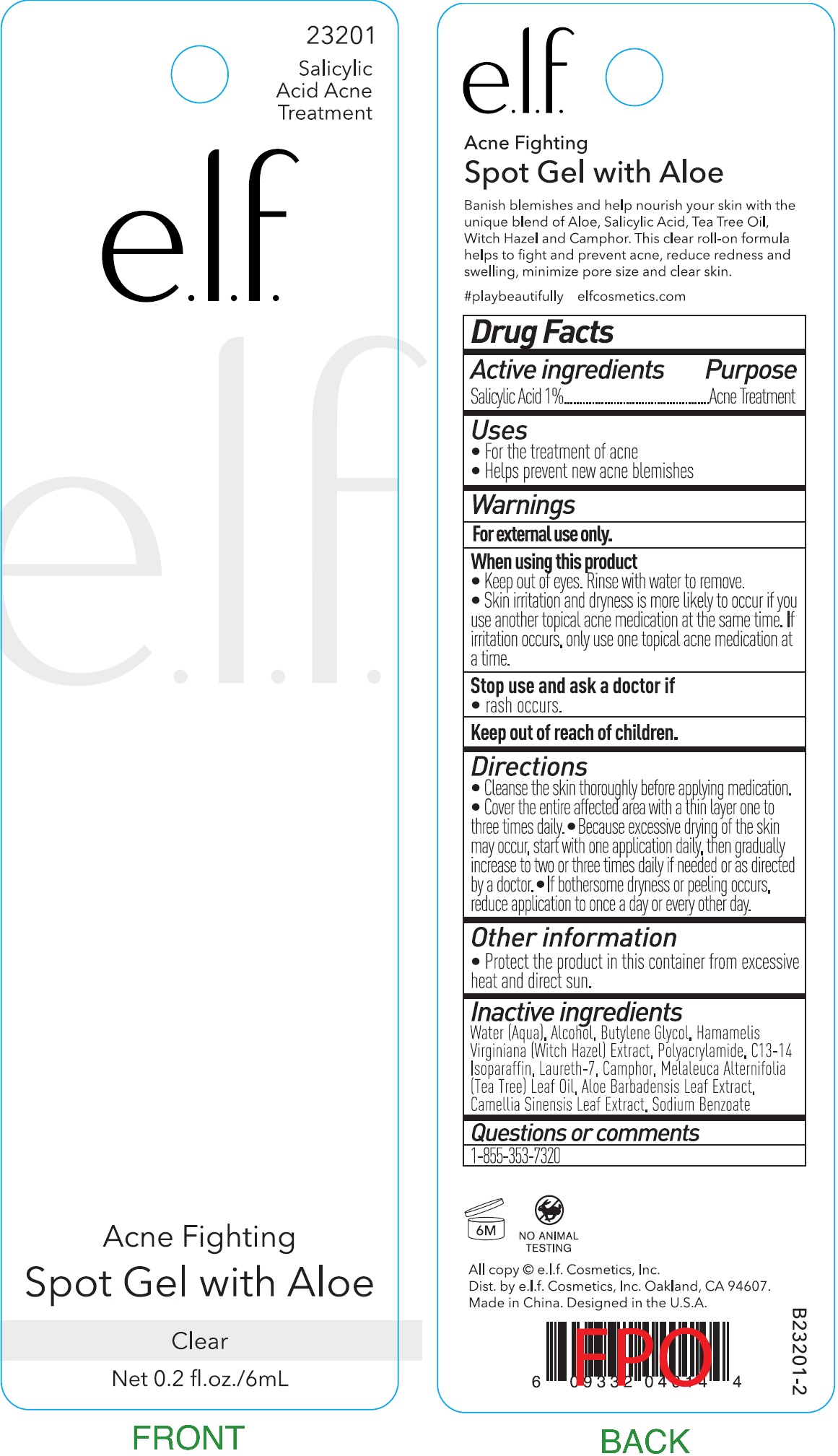 DRUG LABEL: Acne Fighting Spot with Aloe clear
NDC: 70412-411 | Form: GEL
Manufacturer: Zhejiang Ayan Biotech Co.,Ltd.
Category: otc | Type: HUMAN OTC DRUG LABEL
Date: 20231121

ACTIVE INGREDIENTS: SALICYLIC ACID 10 mg/1 mL
INACTIVE INGREDIENTS: WATER; ALCOHOL; BUTYLENE GLYCOL; HAMAMELIS VIRGINIANA TOP; C13-14 ISOPARAFFIN; LAURETH-7; TEA TREE OIL; ALOE VERA LEAF; GREEN TEA LEAF; SODIUM BENZOATE

Acne Fighting Spot Gel with Aloe clear

Active ingredients

Salicylic Acid 1%

Purpose

Acne Treatment

Uses

- For the treatment of acne
- Helps prevent new acne blemishes

Warnings

For external use only.

When using this product

- Keep out of eyes. Rinse with water to remove.
- Skin irritation and dryness is more likely to occur if you use another topical acne medication at the same time. If irritation occurs. only use one topical acne medication at a time.

Stop use and ask a doctor if

- rash occurs.

Directions

- Cleanse the skin thoroughly before applying medication.
- Cover the entire affected area with a thin layer one to three times daily.
- Because excessive drying of the skin may occur, start with one application daily, then gradually increase to two or three times daily if needed or as directed by a doctor.
- If bothersome dryness or peeling occurs, reduce application to once a day or every other day.

Other Information

- Protect the product in this container from excessive heat and direct sun.

Inactive ingredients

Water (Aqua), Alcohol, Butylene Glycol, Hamamelis Virginiana (Witch Hazel) Extract, Polyacrylamide, C13-14 Isoparaffin, Laureth-7, Camphor, Melaleuca Alternifolia (Tea Tree) Leaf Oil, Aloe Barbadensis Leaf Extract, Camellia Sinensis Leaf Extract, Sodium Benzoate

Questions or comments

1-855-353-7320